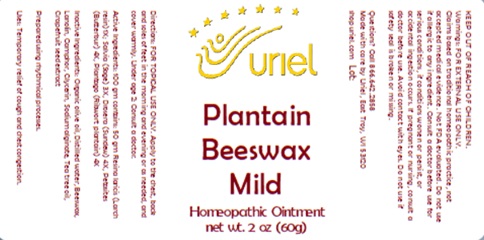 DRUG LABEL: Plantain Beeswax Mild
NDC: 48951-8355 | Form: OINTMENT
Manufacturer: Uriel Pharmacy Inc.
Category: homeopathic | Type: HUMAN OTC DRUG LABEL
Date: 20241115

ACTIVE INGREDIENTS: PETASITES HYBRIDUS ROOT 4 [hp_X]/1 g; PLANTAGO MAJOR LEAF 4 [hp_X]/1 g; LARIX DECIDUA RESIN 1 [hp_X]/1 g; SAGE 3 [hp_X]/1 g; DROSERA ROTUNDIFOLIA 4 [hp_X]/1 g
INACTIVE INGREDIENTS: CAMPHOR (NATURAL); GLYCERIN; TEA TREE OIL; CITRUS PARADISI SEED; OLIVE OIL; WATER; YELLOW WAX; LANOLIN; SORBIC ACID; SODIUM ALGINATE

Plantain Beeswax Mild

INDICATIONS AND USAGE

Directions: FOR TOPICAL USE ONLY.

DOSAGE AND ADMINISTRATION

Apply to the chest, back and soles of feet in the morning and evening or as needed, and cover warmly. Under age 2: Consult a doctor.

ACTIVE INGREDIENT

Active Ingredients: 100 gm contains: 50 gm Resina laricis (Larch resin) 1X; Salvia (Sage) 3X, Drosera (Sundew) 4X, Petasites (Butterbur) 4X, Plantago (Ribwort plantain) 4X

INACTIVE INGREDIENT

Inactive Ingredients: Organic olive oil, Distilled water, Beeswax, Lanolin, Camphor, Glycerin, Sodium alginate, Sorbic acid, Tea tree oil, Grapefruit seed extract

Prepared using rhythmical processes.

PURPOSE

Uses: Temporary relief of cough and chest congestion.

KEEP OUT OF REACH OF CHILDREN.

Warnings: FOR EXTERNAL USE ONLY.
Claims based on traditional homeopathic practice, not accepted medical evidence. Not FDA evaluated. Do not use if allergic to any ingredient. Consult a doctor before use for serious conditions, if conditions worsen or persist, or accidental ingestion occurs. If pregnant or nursing, consult a doctor before use. Avoid contact with eyes. Do not use if safety seal is broken or missing.

Questions? Call 866.642.2858
Made with care by Uriel, East Troy, WI 53120
shopuriel.com Lot: